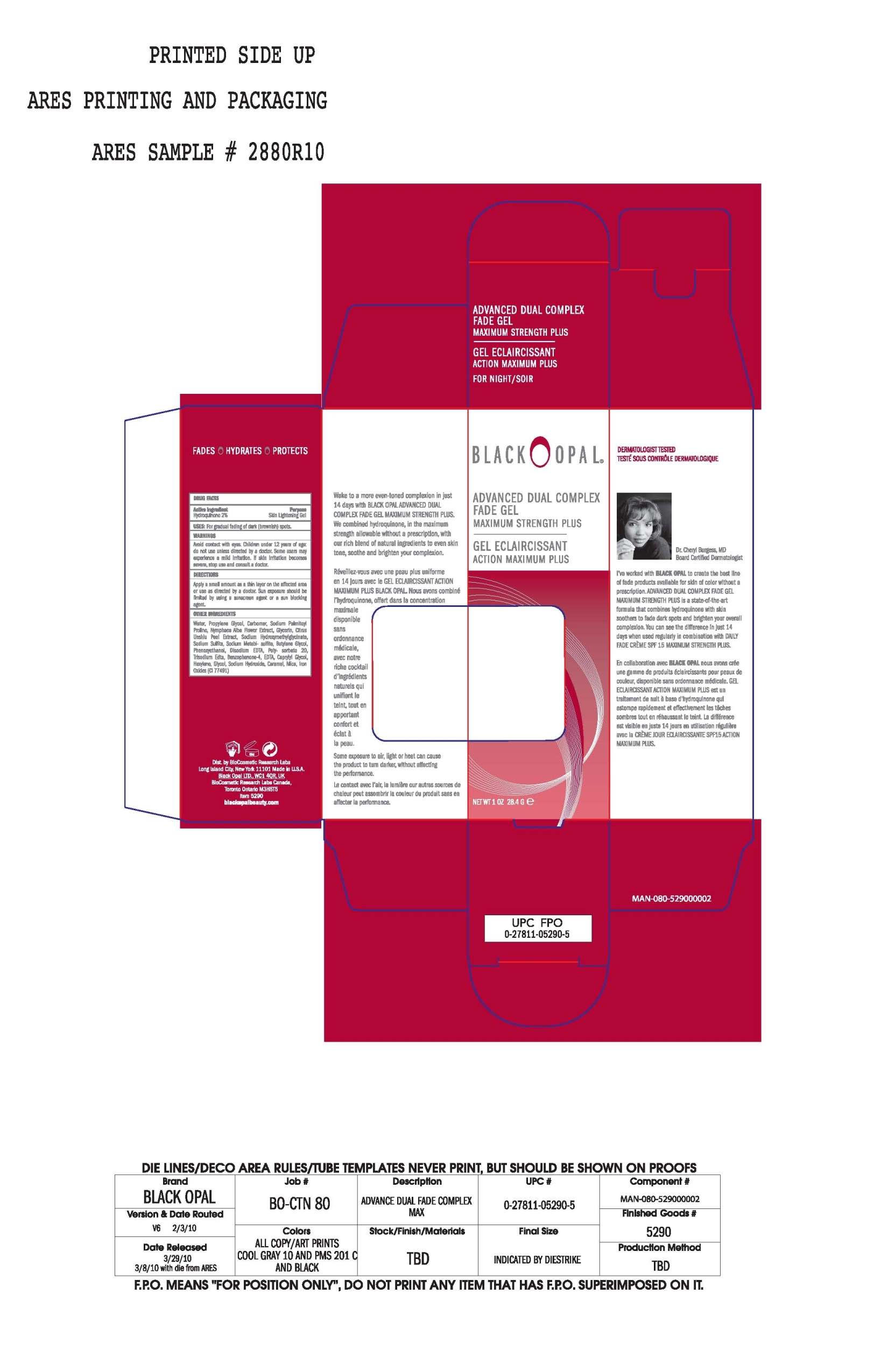 DRUG LABEL: Advanced Dual Complex Fade
NDC: 59735-310 | Form: GEL
Manufacturer: Biocosmetic Research Labs
Category: otc | Type: HUMAN OTC DRUG LABEL
Date: 20090225

ACTIVE INGREDIENTS: Hydroquinone 2 g/100 g

Advanced Dual Complex Fade Gel Maximum Strength Plus

Active Ingredient:

Hydroquinone 2%

Purpose:

Skin Lightening Gel

Uses:

For gradual fading of dark (brownish) spots

Warnings:

Avoid contact with eyes. Children under 12 years of age; Do not use unless directed by a doctor.

STOP USE

Some users may experience a mild irritation. If skin irritation becomes severe, stop use and consult a doctor.

Directions:

Apply a small amount as a thin layer on the affected area or use as directed by a doctor. Sun exposure should be limited by using a sunscreen agent or a sun blocking agent.

INACTIVE INGREDIENT

Other Ingredients:

Water, Propylene Glycol, Carbomer, Sodium Palmitoyl Proline, Nymphaea Alba Flower Extract, glycerin, Citrus Unshiu Peel Extract, Sodium Hydroxymethylglycinate,Sodium Sulfite, Sodium Metabisulfite, Butylene Glycol, Phenoxyethanol, Disodium EDTA, Polysorbate 20, Trisodium EDTA, Benzophenone-4, EDTA, Caprylyl Glycol, Hexylene Glycol, Sodium Hydroxide, Caramel, Mica, Iron Oxides (CI 77491)